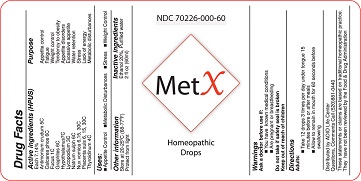 DRUG LABEL: MetX
NDC: 61727-001 | Form: SOLUTION/ DROPS
Manufacturer: Homeocare Laboratories Inc.
Category: homeopathic | Type: HUMAN OTC DRUG LABEL
Date: 20160307

ACTIVE INGREDIENTS: THYROID, UNSPECIFIED 4 [hp_C]/60 mL; FUCUS SERRATUS 1 [hp_C]/60 mL; TRIBASIC CALCIUM PHOSPHATE 6 [hp_C]/60 mL; GRAPHITE 6 [hp_C]/60 mL; SODIUM SULFIDE 6 [hp_C]/60 mL; LYCOPODIUM CLAVATUM SPORE 3 [hp_C]/60 mL; SUS SCROFA PLACENTA 30 [hp_C]/60 mL; ANTIMONY TRISULFIDE 5 [hp_C]/60 mL; BOS TAURUS HYPOTHALAMUS 7 [hp_C]/60 mL
INACTIVE INGREDIENTS: 1-(4-CHLOROPHENYL)-1-PHENYLETHANOL; WATER

PURPOSE

Appetite Control

Fatigue

Tendency to obesity

Weight control

Appetite disorders

Excessive appetite

water retention

Stress

Lack of energy

Metabolic disturbances

USAGE AND DIRECTIONS

Adults

Take 12 drops 3 times per day under tongue 15 minutes before or after meal

Allow to remain in mouth for 60 seconds before swallowing

WARNING

Ask a doctor befre use if you have known medical conditions,

pregnant or breastfeeding

Do not take if safety seal is broken

KEEP OUT OF REACH OF CHILDREN

QUESTIONS AND COMMENTS

CALL - (520) 881-0440

ACTIVE INGREDIENT

Antimonium crudum

Calcarea phos

Fucus

Graphites

Hypothalamus

Lycopodium

Natrum sulph

Nux vomica

Placenta suis

Thyroidinum

INACTIVE INGREDIENT

Ethanol

Purified Water

DOSAGE & ADMINISTRATION

Adults
Take 12 drops 3 times per day under tongue 15 minutes before or after meal
Allow to remain in mouth for 60 seconds before swallowing